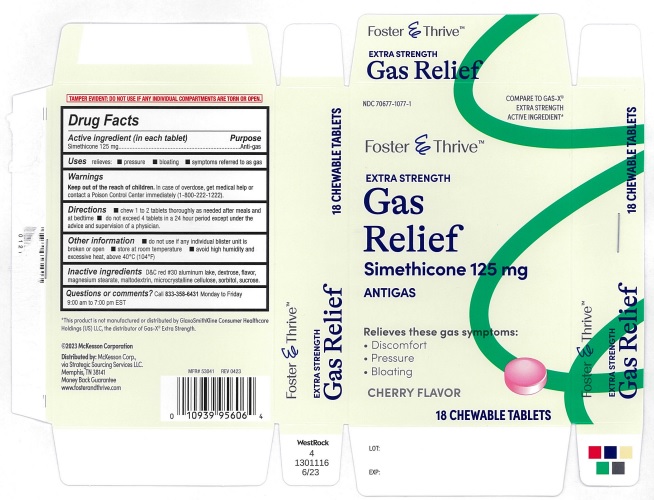 DRUG LABEL: Foster and Thrive Extra Strength Gas Relief Cherry
NDC: 70677-1077 | Form: TABLET, CHEWABLE
Manufacturer: Strategic Sourcing Services LLC
Category: otc | Type: Human OTC Drug Label
Date: 20241213

ACTIVE INGREDIENTS: DIMETHICONE 125 mg/1 1
INACTIVE INGREDIENTS: D&C RED NO. 30; MAGNESIUM STEARATE; CELLULOSE, MICROCRYSTALLINE; SORBITOL; SUCROSE; MALTODEXTRIN; DEXTROSE, UNSPECIFIED FORM

Foster and Thrive Extra strength Gas Relief Cherry

ACTIVE INGREDIENT(in each tablet)

Simethicone 125 mg

PURPOSE

Anti-gas

USE(S)

relieves:

- pressure
- bloating
- symptoms referred to as gas

WARNINGS

.

KEEP OUT OF REACH OF CHILDREN.

In case of overdose, get medical help or contact a poison control center immediately (1-800-222-1222).

DIRECTIONS

- chew 1 to 2 tablets thoroughly as needed after meals and at bedtime
- do not exceed 4 tablets in a 24 hour period except under the advice and supervision of a physician.

OTHER INFORMATION

- do not use if any individual blister unit is broken or open
- store at room temperature
- avoid high humidity and excessive heat, above 40ºC (104ºF)

INACTIVE INGREDIENTS

D&C red # 30 aluminum lake, dextrose, flavor, magnesium stearate, maltodextrin, microcrystalline cellulose, sorbitol, sucrose.

QUESTIONS OR COMMENTS?

Call 833-358-6431 Monday to Friday 9:00 am to 7:00 pm EST

PRINCIPAL DISPLAY PANEL

NDC 70677-1077-1

COMPARE TO GAS-X® EXTRA STRENGTH ACTIVE INGREDIENT*

Foster & Thrive TM

EXTRA STRENGTH

Gas Relief

Simethicone 125 mg

ANTIGAS

Relieves these gas symptoms:

- Discomfort
- Pressure
- Bloating

CHERRY FLAVOR

18 CHEWABLE TABLETS